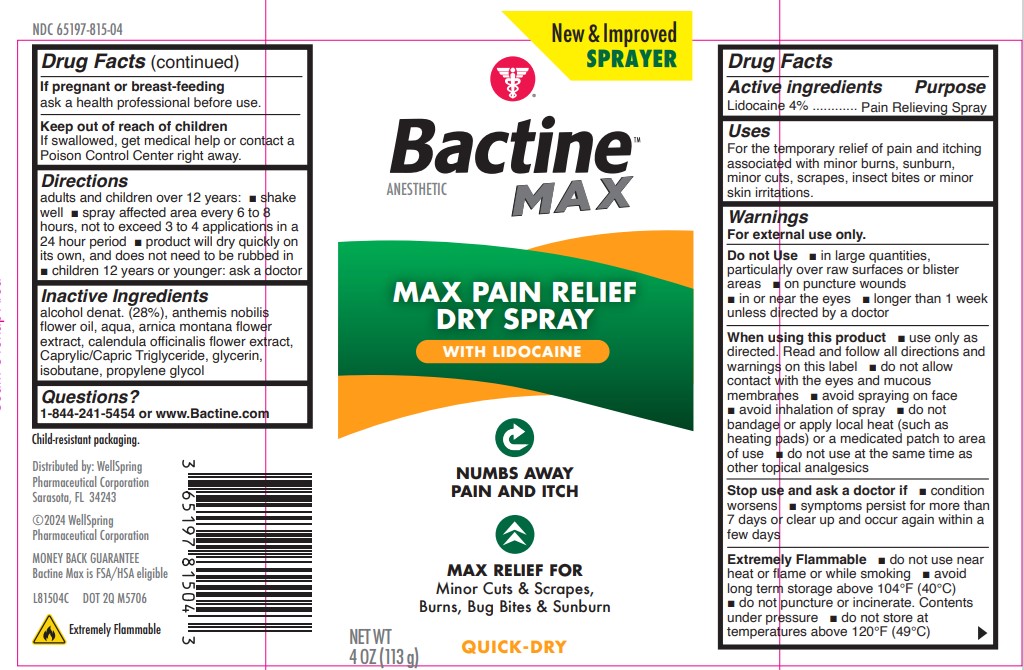 DRUG LABEL: Bactine Max Dry
NDC: 65197-815 | Form: SPRAY
Manufacturer: WellSpring Pharmaceutical Corporation
Category: otc | Type: HUMAN OTC DRUG LABEL
Date: 20221227

ACTIVE INGREDIENTS: LIDOCAINE HYDROCHLORIDE 4 g/100 g
INACTIVE INGREDIENTS: CHAMAEMELUM NOBILE FLOWER OIL; ARNICA MONTANA FLOWER; CALENDULA OFFICINALIS FLOWER; WATER; MEDIUM-CHAIN TRIGLYCERIDES; GLYCERIN; ISOBUTANE; PROPYLENE GLYCOL; ALCOHOL

Bactine® Max Pain Relieving Cleansing Spray

Drug Facts

Active Ingredients

Lidocaine 4%

Purpose

Pain Relieving Spray

Uses

For the temporary relief of pain and itching associated with minor burns, sunburn, minor cuts, scrapes, insect bites or minor skin irritations.

Warnings

For external use only

Do not Use

■ in large quantities, particularly over raw surfaces or blister areas

■ on puncture wounds

■ in or near the eyes

■ longer than 1 week unless directed by a doctor

When using this product

■ use only as directed. Read and follow all directions and warnings on this label.

■ do not allow contact with the eyes and mucous membranes

■ avoid spraying on face

■ avoid inhalation of spray

■ do not bandage or apply local heat (such as heating pads) or a medicated patch to area of use

■ do not use at the same time as other topical analgesics

Stop use and ask a doctor if

- condition worsens
- symptoms persist for more than 7 days, or clear up and occur again within a few days

Extremely Flammable

■ do not use near heat or flame or while smoking

■ avoid long term storage above 104°F (40°C)

■ do not puncture or incinerate. Contents under pressure.

■ do not store at temperatures above 120°F (49°C)

If pregnant or breast-feeding

ask a health professional before use.

Keep out of reach of children.

If swallowed, get medical help or contact a Poison Control Center right away.

Directions

■ adults and children over 12 years:

■ spray affected area every 6 to 8 hours, not to exceed 3 to 4 applications in a 24 hour period

■ product will dry quickly on its own, and does not need to be rubbed in

■ children 12 years or younger: ask a doctor

SAFE HANDLING WARNING

Child-resistant packaging. Replace cap after each use

Inactive ingredients

alcohol denat. (28 %)

anthemis nobilis flower oil

aqua

arnica montana flower extract

calendula officinalis flower extract

Caprylic/Capric Triglyceride

glycerin

isobutane

propylene glycol

Questions?

1-844-241-5454 or www.bactine.com

Distributed by:

WellSpring Pharmaceutical Corporation

Sarasota, FL 34243

©2022 Wellspring

Pharmaceutical Corporation

MONEYBACK GUARANTEE

Bactine max is FSA/HSA eligible

DOT 2Q M5706

Extremely Flammable

PRINCIPAL DISPLAY PANEL

NEW

NDC 65197-815-04

Bactine MAX

LIDOCAINE Dry Spray

Anesthetic

NUMBS AWAY PAIN AND ITCH

MAX RELIEF FOR Minor Cuts & Scrapes, Burns, Bug bites & Sunburn

QUICK-DRY

4oz (113g)

Bactine Dry Spray 113g